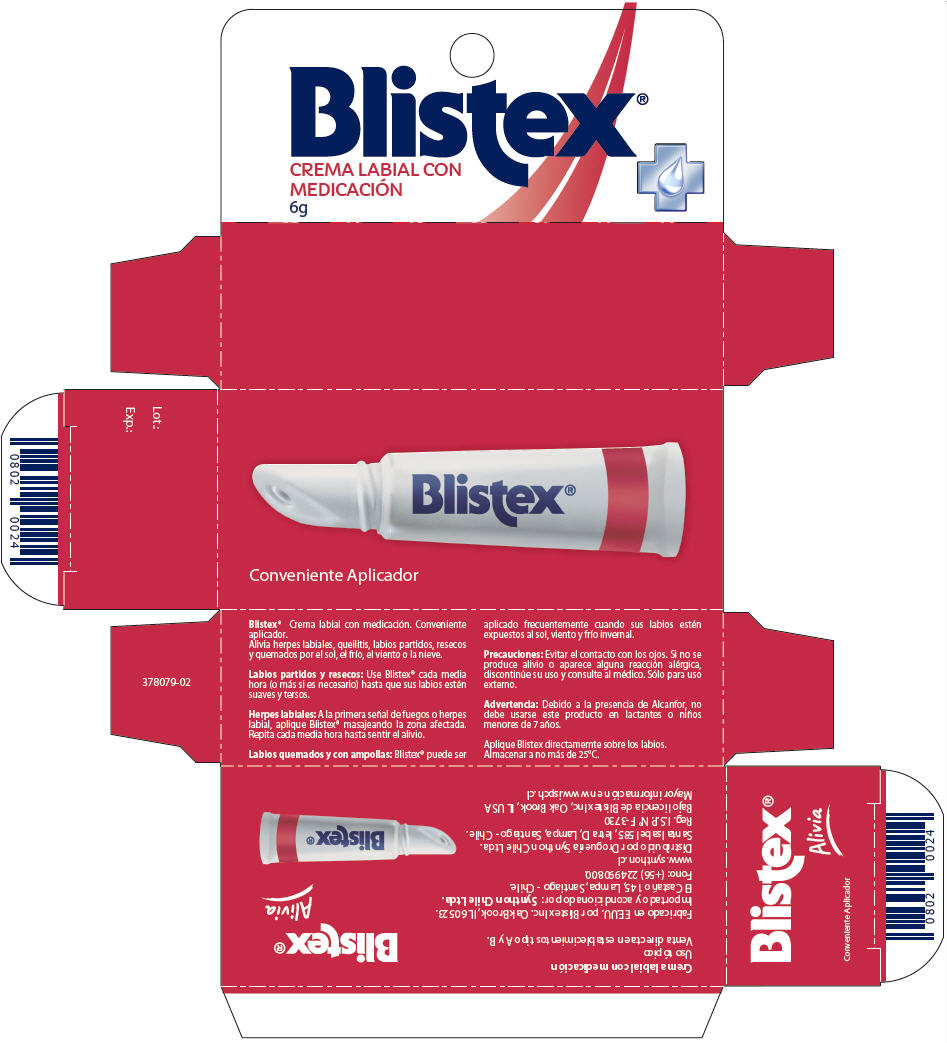 DRUG LABEL: Blistex con Medicacion Crema Labial
NDC: 10157-9926 | Form: STICK
Manufacturer: Blistex Inc.
Category: otc | Type: HUMAN OTC DRUG LABEL
Date: 20170623

ACTIVE INGREDIENTS: CAMPHOR (SYNTHETIC) 1 g/100 g; PHENOL 0.45 g/100 g
INACTIVE INGREDIENTS: MINERAL OIL; WATER; YELLOW WAX; PARAFFIN; PETROLATUM; LANOLIN; POLYGLYCERYL-3 DIISOSTEARATE; ALCOHOL; GLYCERIN; CALCIUM STEAROYL LACTYLATE; SILICON DIOXIDE; METHYL SALICYLATE; GLYCERYL MONOSTEARATE; LEVOMENTHOL; CETYL ALCOHOL; AMMONIA; CALCIUM HYDROXIDE; SODIUM HYDROXIDE

Blistex® con Medicación Crema Labial

PRINCIPAL DISPLAY PANEL - 6g Tube Carton

Conveniente Aplicador